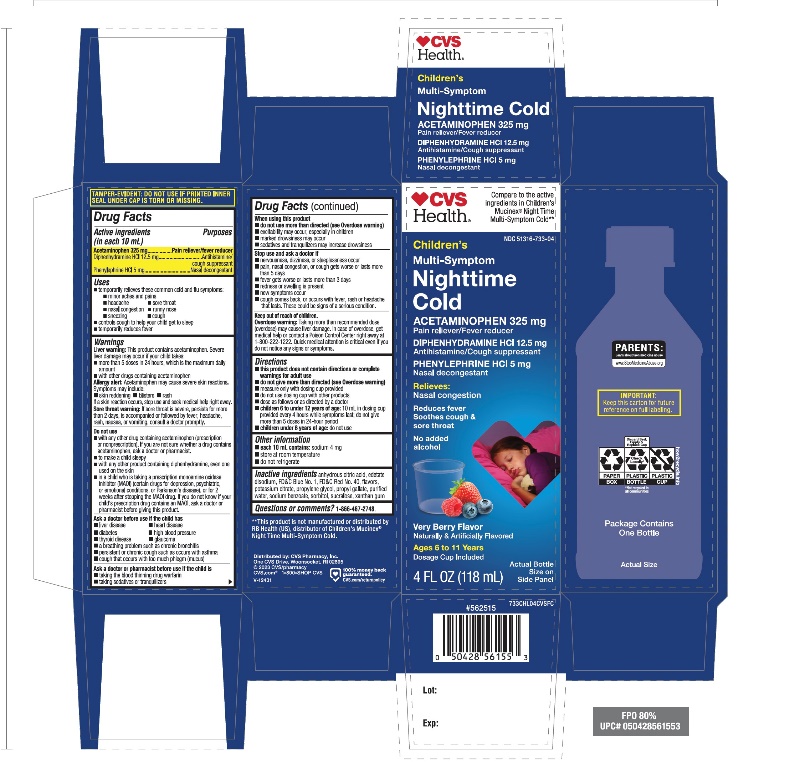 DRUG LABEL: CVS Childrens Nighttime Multi Symptom Cold
NDC: 51316-733 | Form: LIQUID
Manufacturer: CVS PHARMACY
Category: otc | Type: HUMAN OTC DRUG LABEL
Date: 20251210

ACTIVE INGREDIENTS: ACETAMINOPHEN 325 mg/10 mL; DIPHENHYDRAMINE HYDROCHLORIDE 12.5 mg/10 mL; PHENYLEPHRINE HYDROCHLORIDE 5 mg/10 mL
INACTIVE INGREDIENTS: ANHYDROUS CITRIC ACID; EDETATE DISODIUM; FD&C BLUE NO. 1; FD&C RED NO. 40; POTASSIUM CITRATE; PROPYLENE GLYCOL; PROPYL GALLATE; WATER; SODIUM BENZOATE; SORBITOL; SUCRALOSE; XANTHAN GUM

CVS Children’s Nighttime Multi-Symptoms Cold 4 FL OZ (180 mL)

Drug Facts

ACTIVE INGREDIENT

PURPOSE

Active ingredients (in each 10 mL) | Purposes
Acetaminophen 325 mg | Pain reliever/fever reducer
Diphenhydramine HCl 12.5 mg | Antihistamine/cough suppressant
Phenylephrine HCl 5 mg | Nasal decongestant

Uses

- temporarily relieves these common cold and flu symptoms:
  - cough
  - nasal congestion
  - minor aches and pains
  - sore throat
  - headache
  - runny nose
  - sneezing
- temporarily reduces fever
- controls cough to help you get to sleep

Warnings

Liver Warning:

This product contains acetaminophen. Severe liver damage may occur if you take:

- more than 5 doses in 24 hours, which is the maximum daily amount
- with other drugs containing acetaminophen

Allergy alert:Acetaminophen may cause severe skin reactions. Symptoms may include:

- Skin reddening
- Blisters
- rash.

If a skin reaction occurs, stop use and seek medical help right away.

Sore throat warning:If sore throat is severe, persists for more than 2 days, is accompanied or followed by fever, headache, rash, nausea, or vomiting, consult a doctor promptly.

Do not use

- with any other drug containing acetaminophen (prescription or nonprescription). If you are not sure whether a drug contains acetaminophen, ask a doctor or pharmacist.
- To make child sleepy
- with any other drug containing diphenhydramine, even one used on the skin
- in a child who is taking a prescription monoamine oxidase inhibitor (MAOI) (certain drugs for depression, psychiatric, or emotional conditions, or Parkinson's disease), or for 2 weeks after stopping the MAOI drug. If you do not know if your prescription drug contains an MAOI, ask a doctor or pharmacist before taking this product.

Ask a doctor before use if the child have

- liver disease
- heart disease
- high blood pressure
- thyroid disease
- diabetes
- glaucoma
- a breathing problem such as chronic bronchitis
- persistent or chronic cough such as occurs with asthma
- cough that occurs with too much phlegm (mucus)

Ask a doctor or pharmacist before use if the child is

- taking the blood thinning drug warfarin
- taking sedatives or tranquilizers

When using this product

- do not use more than directed (see Overdose warning)
- excitability may occur, especially in children
- marked drowsiness may occur
- sedatives and tranquilizers may increase drowsiness

Stop use and ask a doctor if

- nervousness, dizziness, or sleeplessness occur
- pain, nasal congestion, or cough gets worse or lasts more than 5 days
- fever gets worse or lasts more than 3 days
- redness or swelling is present
- new symptoms occur
- cough comes back, or occurs with fever, rash, or headache that lasts. These could be signs of a serious condition.

Keep out of reach of children.

Overdose warning:

Taking more than the recommended dose (overdose) may cause liver damage. In case of overdose, get medical help or contact a Poison Control Center right away 1-800-222-1222. Quick medical attention is critical for adults as well as for children, even if you do not notice any signs or symptoms.

Directions

- this product does not contain directions or complete warnings for adult use
- do not give more than directed (see Overdose warning)
- measure only with dosing cup provided
- do not use dosing cup with other products
- dose as follows or as directed by a doctor
- children 6 years to 12 years of age: 10 mL in dosing cup provided every 4 hours while symptoms last; do not give more than 5 doses in 24-hours period
- children under 6 years of age: do not use

Other information

- each 10 mL contains: sodium 4 mg
- store at room temperature
- do not refrigerate

Inactive ingredients

anhydrous citric acid, edetate disodium, FD&C blue #1, FD&C red #40, natural and artificial flavor, potassium citrate, propylene glycol, propyl gallate, purified water, sodium benzoate, sorbitol, sucralose, xanthan gum.

Questions or comments?

1-866-467-2748

PRINCIPAL DISPLAY PANEL

Compare to the active ingredients in Children’s Mucinex®Night Time Multi-Symptom Cold

NDC# 51316-733-04

Children’s

Night Time Muti-Symptom Cold

- AcetaminophenPain Reliever/Fever Reducer
  Diphenhydramine HCl Antihistamine/Cough Suppressant
  Phenylephrine HCl Nasal Decongestant

Relieves Stuffy Nose

Controls Cough

Relieves Fever & Sore Throat

Relieves Runny Nose & Sneezing

Dosing Cup Included

For Ages 6 & Over

Very Berry Flavor

Naturally and Artificially Flavored

4 FL OZ (118 mL)

*This product is not manufactured or distributed by RB Health (US), distributor Children’s Mucinex®Nighttime Multi-Symptoms Cold..

TAMPER EVIDENT: DO NOT USE IF PRINTED SEAL UNDER CAP IS BROKEN OR MISSING.

Distributed by: